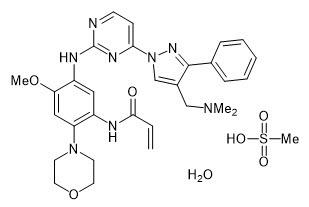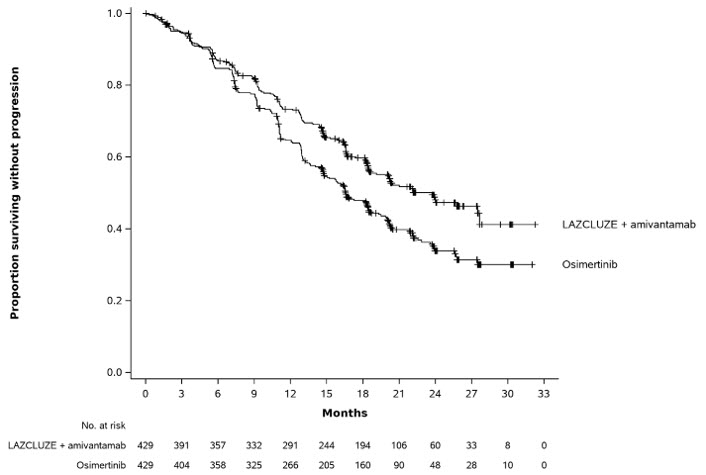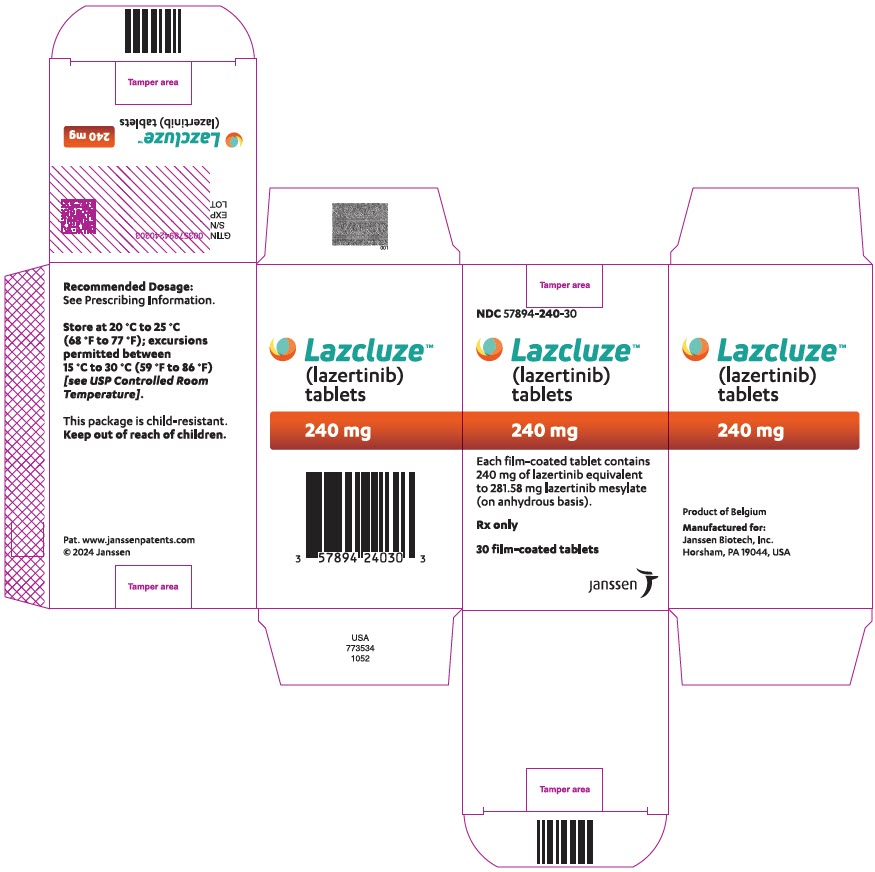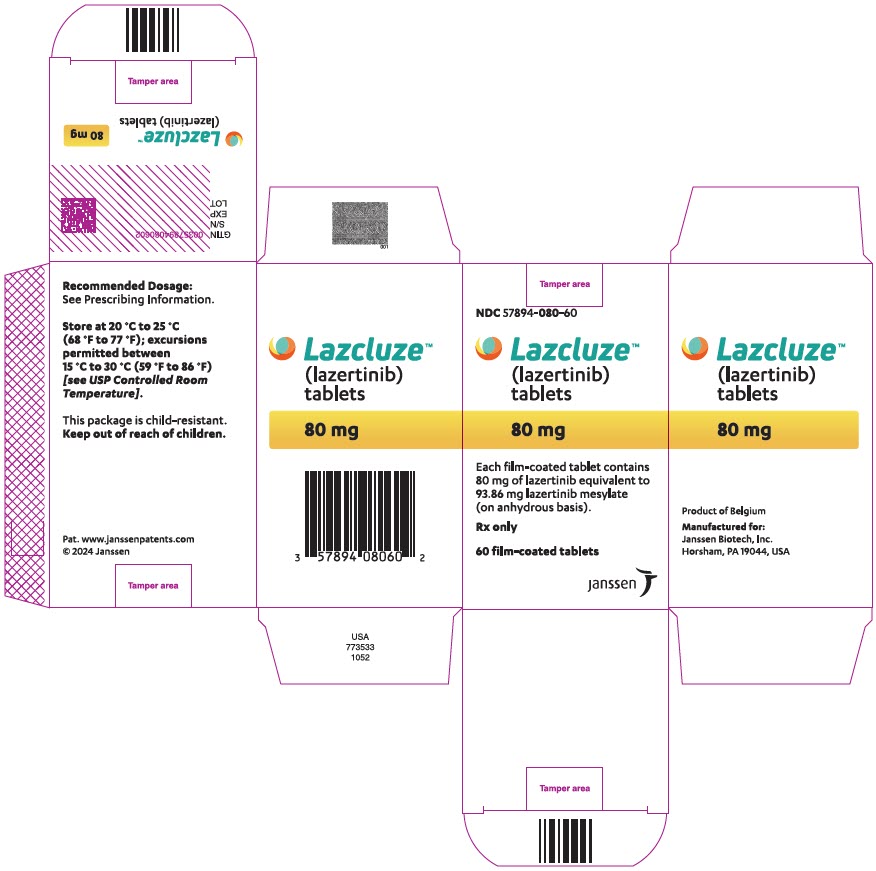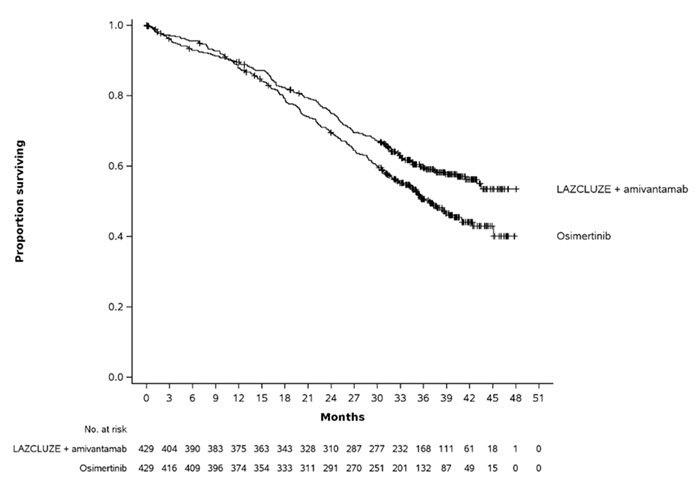 DRUG LABEL: LAZCLUZE
NDC: 57894-240 | Form: TABLET, FILM COATED
Manufacturer: Janssen Biotech, Inc.
Category: prescription | Type: HUMAN PRESCRIPTION DRUG LABEL
Date: 20251121

ACTIVE INGREDIENTS: LAZERTINIB 240 mg/1 1
INACTIVE INGREDIENTS: FERRIC OXIDE RED; SILICON DIOXIDE; CROSCARMELLOSE SODIUM; MICROCRYSTALLINE CELLULOSE; MANNITOL; MAGNESIUM STEARATE; POLYETHYLENE GLYCOL, UNSPECIFIED; POLYVINYL ALCOHOL, UNSPECIFIED; GLYCERYL MONOCAPRYLOCAPRATE; TITANIUM DIOXIDE; TALC; FERROSOFERRIC OXIDE

HIGHLIGHTS OF PRESCRIBING INFORMATION

These highlights do not include all the information needed to use LAZCLUZE safely and effectively. See full prescribing information for LAZCLUZE.
LAZCLUZE®(lazertinib) tablets, for oral use
Initial U.S. Approval: 2024

RECENT MAJOR CHANGES

Dosage and Administration (2.3) | 11/2025
Warnings and Precautions (5.3) | 11/2025

1 INDICATIONS AND USAGE

LAZCLUZE is a kinase inhibitor indicated in combination with amivantamab for the first-line treatment of adult patients with locally advanced or metastatic non-small cell lung cancer (NSCLC) with epidermal growth factor receptor (EGFR) exon 19 deletions or exon 21 L858R substitution mutations, as detected by an FDA-approved test. (1)

2 DOSAGE AND ADMINISTRATION

- The recommended dosage of LAZCLUZE is 240 mg orally once daily with or without food, given in combination with amivantamab. (2.2)
- Continue treatment until disease progression or unacceptable toxicity. (2.2)
- Administer LAZCLUZE any time prior to amivantamab when given on the same day. (2.2)
- Refer to the amivantamab prescribing information for recommended amivantamab dosing information. (2.2)
- Administer prophylactic and concomitant medications to reduce the risk of dermatologic adverse reactions. (2.3)
- Administer anticoagulant prophylaxis to reduce the risk of venous thromboembolic events (VTE) for the first four months of treatment. (2.3)

3 DOSAGE FORMS AND STRENGTHS

Tablets:80 mg and 240 mg. (3)

4 CONTRAINDICATIONS

None. (4)

5 WARNINGS AND PRECAUTIONS

- Venous Thromboembolic Events (VTE):Prophylactic anticoagulation is recommended for the first four months of treatment. Monitor for signs and symptoms of VTE and treat as medically appropriate. Withhold LAZCLUZE and amivantamab based on severity. Once anticoagulant treatment has been initiated, resume LAZCLUZE and amivantamab at the same dose at the discretion of the healthcare provider. Permanently discontinue amivantamab and continue LAZCLUZE for recurrent VTE despite therapeutic anticoagulation. (2.3, 2.4, 5.1)
- Interstitial Lung Disease (ILD)/Pneumonitis: Monitor for new or worsening symptoms indicative of ILD/pneumonitis. Withhold LAZCLUZE and amivantamab in patients with suspected ILD/pneumonitis and permanently discontinue if ILD/pneumonitis is confirmed. (2.4, 5.2)
- Dermatologic Adverse Reactions: Can cause severe rash including acneiform dermatitis. At treatment initiation, prophylactic and concomitant medications are recommended. Withhold, reduce the dose or permanently discontinue LAZCLUZE and amivantamab based on severity. (2.3, 2.4, 5.3)
- Ocular Adverse Reactions: Promptly refer patients with new or worsening signs and symptoms of ocular adverse reactions, including keratitis, to an ophthalmologist for evaluation. Withhold, reduce the dose, or permanently discontinue amivantamab and continue LAZCLUZE based on severity. (5.4)
- Embryo-Fetal Toxicity: Can cause fetal harm. Advise patients of reproductive potential of the potential risk to a fetus and to use effective contraception. (5.5, 8.1, 8.3)

6 ADVERSE REACTIONS

LAZCLUZE in Combination with Amivantamab

- The most common adverse reactions (≥ 20%) were rash, nail toxicity, infusion-related reaction (amivantamab), musculoskeletal pain, edema, stomatitis, VTE, paresthesia, fatigue, diarrhea, constipation, COVID-19, hemorrhage, dry skin, decreased appetite, pruritus, and nausea. (6.1)
- The most common Grade 3 or 4 laboratory abnormalities (≥ 2%) were decreased albumin, decreased sodium, increased ALT, decreased potassium, decreased hemoglobin, increased AST, increased GGT, and increased magnesium. (6.1)

To report SUSPECTED ADVERSE REACTIONS, contact Janssen Biotech, Inc. at 1-800-526-7736 or FDA at 1-800-FDA-1088 or www.fda.gov/medwatch.

7 DRUG INTERACTIONS

Strong and moderate CYP3A4 inducers:Avoid concomitant use. (7.1)

8 USE IN SPECIFIC POPULATIONS

Lactation:Advise not to breastfeed. (8.2)

FULL PRESCRIBING INFORMATION

1 INDICATIONS AND USAGE

LAZCLUZE, in combination with amivantamab, is indicated for the first-line treatment of adult patients with locally advanced or metastatic non-small cell lung cancer (NSCLC) with epidermal growth factor receptor (EGFR) exon 19 deletions or exon 21 L858R substitution mutations, as detected by an FDA-approved test [see Dosage and Administration (2.1)] .

2 DOSAGE AND ADMINISTRATION

2.1 Patient Selection

Select patients for the first-line treatment of NSCLC with LAZCLUZE, in combination with amivantamab, based on the presence of EGFR exon 19 deletions or exon 21 L858R substitution mutations in tumor or plasma specimens [see Clinical Studies (14)] . If these mutations are not detected in a plasma specimen, test tumor tissue. Information on FDA-approved tests is available at: http://www.fda.gov/CompanionDiagnostics.

2.2 Recommended Dosage and Administration

Recommended Dosage and Administration

The recommended dosage of LAZCLUZE is 240 mg orally once daily administered in combination with amivantamab, with or without food. Swallow LAZCLUZE tablets whole. Do not crush, split, or chew. Continue treatment until disease progression or unacceptable toxicity.

Administer LAZCLUZE any time prior to amivantamab when given on the same day. Refer to the amivantamab prescribing information for recommended amivantamab dosing information.

Missed Dose

If a patient misses a dose of LAZCLUZE within 12 hours, instruct patients to take the missed dose. If more than 12 hours has passed since the dose was to be given, instruct the patient to take the next dose at its scheduled time.

Vomiting

If vomiting occurs any time after taking LAZCLUZE, instruct the patient to take the next dose at its next regularly scheduled time.

2.3 Prophylactic and Concomitant Medications

Venous Thromboembolic Events

When initiating treatment with LAZCLUZE in combination with amivantamab, administer anticoagulant prophylaxis to reduce the risk of venous thromboembolic events (VTE) for the first four months of treatment [see Warnings and Precautions (5.1)]. If there are no signs or symptoms of VTE during the first four months of treatment, consider discontinuation of anticoagulant prophylaxis at the discretion of the healthcare provider.

Dermatologic Adverse Reactions

When initiating treatment with LAZCLUZE in combination with amivantamab, prophylactic and concomitant medications are recommended to reduce the risk and severity of dermatologic adverse reactions [see Warnings and Precautions (5.3)].

- Administer an oral antibiotic (doxycycline or minocycline, 100 mg orally twice daily) starting on Day 1 for the first 12 weeks of treatment.
- After completion of oral antibiotic treatment, administer antibiotic lotion to the scalp (clindamycin 1% topical once daily) for the next 9 months of treatment.
- Administer non-comedogenic skin moisturizer (ceramide-based or other formulations that provide long-lasting skin hydration and exclude drying agents) on the face and whole body (except scalp).
- Wash hands and feet with 4% chlorhexidine solution once daily.
- Limit sun exposure during and for 2 months after treatment. Advise patients to wear protective clothing and use broad-spectrum UVA/UVB sunscreen to reduce the risk of dermatologic adverse reactions.

2.4 Dosage Modifications for Adverse Reactions

The recommended LAZCLUZE dose reductions for adverse reactions are presented in Table 1.

Table 1: Recommended Dose Reductions for Adverse Reactions for LAZCLUZE
Dose at which the adverse reaction occurred | 1st Dose Reduction | 2nd Dose Reduction | 3rd Dose Reduction
240 mg once daily (one 240 mg tablet) | 160 mg once daily (two 80 mg tablets) | 80 mg once daily (one 80 mg tablet) | Discontinue LAZCLUZE

The recommended management and dosage modifications of LAZCLUZE for specific adverse reactions are presented in Table 2. Refer to the amivantamab prescribing information for information about dosage modifications for amivantamab.

Table 2: Recommended Management and Dosage Modifications for Adverse Reactions
Adverse Reaction | Severity | Dosage Modification
Venous Thromboembolic Events (VTE) [see Warnings and Precautions (5.1)] | Grade 2 or 3 | - Withhold LAZCLUZE and amivantamab. - Administer anticoagulant treatment as clinically indicated. - Once anticoagulant treatment has been initiated, resume LAZCLUZE and amivantamab at the same dose level, at the discretion of the healthcare provider.
Venous Thromboembolic Events (VTE) [see Warnings and Precautions (5.1)] | Grade 4 or recurrent Grade 2 or 3 despite therapeutic level anticoagulation | - Withhold LAZCLUZE and permanently discontinue amivantamab. - Administer anticoagulant treatment as clinically indicated. - Once anticoagulant treatment has been initiated, treatment can continue with LAZCLUZE at the same dose level at the discretion of the healthcare provider.
Interstitial Lung Disease (ILD)/Pneumonitis [see Warnings and Precautions (5.2)] | Any Grade | - Withhold LAZCLUZE and amivantamab if ILD/pneumonitis is suspected. - Permanently discontinue LAZCLUZE and amivantamab if ILD/pneumonitis is confirmed.
Dermatologic Adverse Reactions (including dermatitis acneiform, pruritus, dry skin) [see Warnings and Precautions (5.3)] | Grade 1 | - Initiate supportive care management as clinically indicated.
Dermatologic Adverse Reactions (including dermatitis acneiform, pruritus, dry skin) [see Warnings and Precautions (5.3)] | Grade 2 | - Initiate supportive care management as clinically indicated. - If there is no improvement after 2 weeks, reduce amivantamab dose and continue LAZCLUZE at the same dose. - Reassess every 2 weeks, if no improvement, reduce LAZCLUZE dose until ≤ Grade 1 (Table 1), then may resume previous dose of LAZCLUZE at the discretion of the healthcare provider.
Dermatologic Adverse Reactions (including dermatitis acneiform, pruritus, dry skin) [see Warnings and Precautions (5.3)] | Grade 3 | - Withhold LAZCLUZE and amivantamab. - Initiate supportive care management as clinically indicated. - Upon recovery to ≤ Grade 2, resume LAZCLUZE at the same dose or consider dose reduction, resume amivantamab at a reduced dose. - If there is no improvement within 2 weeks, permanently discontinue both LAZCLUZE and amivantamab.
Dermatologic Adverse Reactions (including dermatitis acneiform, pruritus, dry skin) [see Warnings and Precautions (5.3)] | Grade 4 (including severe bullous, blistering or exfoliating skin conditions) | - Initiate supportive care management as clinically indicated. - Permanently discontinue amivantamab. - Withhold LAZCLUZE until recovery ≤ Grade 2 or baseline. - Upon recovery to ≤ Grade 2, resume LAZCLUZE at a reduced dose at the discretion of the healthcare provider.
Other Adverse Reactions [see Adverse Reactions (6.1)] | Grade 3–4 | - Withhold LAZCLUZE and amivantamab until the adverse reaction resolves to ≤ Grade 1 or baseline. - Resume both drugs at a reduced dose or LAZCLUZE alone. - Consider permanently discontinuing both LAZCLUZE and amivantamab if recovery does not occur within 4 weeks.

3 DOSAGE FORMS AND STRENGTHS

Tablets

- 80 mg tablets: yellow, oval film-coated tablet, debossed with "LZ" on one side and "80" on the other side. Each tablet contains 80 mg of lazertinib.
- 240 mg tablets: reddish purple, oval film-coated tablet, debossed with "LZ" on one side and "240" on the other side. Each tablet contains 240 mg of lazertinib.

4 CONTRAINDICATIONS

None.

5 WARNINGS AND PRECAUTIONS

5.1 Venous Thromboembolic Events

LAZCLUZE in combination with amivantamab can cause serious and fatal venous thromboembolic events (VTE), including deep venous thrombosis (DVT) and pulmonary embolism (PE). The majority of these events occurred during the first four months of therapy [see Adverse Reactions (6.1)] .

In MARIPOSA [see Adverse Reactions (6.1)] , VTE occurred in 36% of patients receiving LAZCLUZE in combination with amivantamab, including Grade 3 in 10% and Grade 4 in 0.5% of patients. On-study VTEs occurred in 1.2% of patients (n=5) while receiving anticoagulation therapy. There were two fatal cases of VTE (0.5%), 7% of patients had VTE leading to dose interruptions of LAZCLUZE, 0.5% of patients had VTE leading to dose reductions of LAZCLUZE, and 1.9% of patients permanently discontinued LAZCLUZE due to VTE. The median time to onset of VTEs was 84 days (range: 6 to 777).

Administer prophylactic anticoagulation for the first four months of treatment [see Dosage and Administration (2.3)] . The use of Vitamin K antagonists is not recommended. Monitor for signs and symptoms of VTE and treat as medically appropriate.

Withhold LAZCLUZE and amivantamab based on severity [see Dosage and Administration (2.4)]. Once anticoagulant treatment has been initiated, resume LAZCLUZE and amivantamab at the same dose level at the discretion of the healthcare provider. In the event of VTE recurrence despite therapeutic anticoagulation, permanently discontinue amivantamab. Continue treatment with LAZCLUZE at the same dose level at the discretion of the healthcare provider [see Dosage and Administration (2.4)] . Refer to the amivantamab prescribing information for recommended amivantamab dosage modification.

5.2 Interstitial Lung Disease (ILD)/Pneumonitis

LAZCLUZE in combination with amivantamab can cause interstitial lung disease (ILD)/pneumonitis.

In MARIPOSA [see Adverse Reactions (6.1)], ILD/pneumonitis occurred in 3.1% of patients treated with LAZCLUZE in combination with amivantamab, including Grade 3 in 1.0% and Grade 4 in 0.2% of patients. There was one fatal case (0.2%) of ILD/pneumonitis and 2.9% of patients permanently discontinued LAZCLUZE and amivantamab due to ILD/pneumonitis [see Adverse Reactions (6.1)].

Monitor patients for new or worsening symptoms indicative of ILD/pneumonitis (e.g., dyspnea, cough, fever). Immediately withhold LAZCLUZE and amivantamab in patients with suspected ILD/pneumonitis and permanently discontinue if ILD/pneumonitis is confirmed [see Dosage and Administration (2.4)].

5.3 Dermatologic Adverse Reactions

LAZCLUZE in combination with amivantamab can cause severe rash including dermatitis acneiform, pruritus and dry skin.

In MARIPOSA [see Adverse Reactions (6.1)] , rash occurred in 86% of patients treated with LAZCLUZE in combination with amivantamab, including Grade 3 in 26% of patients. The median time to onset of rash was 14 days (range: 1 to 556 days). Rash leading to dose reduction of LAZCLUZE occurred in 19% of patients, rash leading to dose interruption of LAZCLUZE occurred in 30% of patients, and LAZCLUZE was permanently discontinued due to rash in 1.7% of patients [see Adverse Reactions (6.1)].

When initiating treatment with LAZCLUZE in combination with amivantamab, prophylactic and concomitant medications are recommended to reduce the risk and severity of dermatologic adverse reactions [see Dosage and Administration (2.3)]. Instruct patients to limit sun exposure during and for 2 months after treatment with LAZCLUZE in combination with amivantamab. Advise patients to wear protective clothing and use broad-spectrum UVA/UVB sunscreen.

If skin reactions develop, administer supportive care including topical corticosteroids and topical and/or oral antibiotics. For Grade 3 reactions, administer oral steroids and consider dermatologic consultation. Promptly refer patients presenting with severe rash, atypical appearance or distribution, or lack of improvement within 2 weeks to a dermatologist. Withhold, reduce the dose or permanently discontinue LAZCLUZE and amivantamab based on severity [see Dosage and Administration (2.4)] .

5.4 Ocular Toxicity

LAZCLUZE, in combination with amivantamab, can cause ocular toxicity, including keratitis.

In MARIPOSA [see Adverse Reactions (6.1)] , ocular toxicity occurred in 16% of patients treated with LAZCLUZE in combination with amivantamab, including Grade 3 or 4 ocular toxicity in 0.7% of patients. Promptly refer patients presenting with new or worsening eye symptoms to an ophthalmologist. Withhold, reduce the dose or permanently discontinue amivantamab and continue LAZCLUZE based on severity [see Dosage and Administration (2.4)] .

5.5 Embryo-Fetal Toxicity

Based on findings from animal studies and its mechanism of action, LAZCLUZE can cause fetal harm when administered to a pregnant woman. In animal reproduction studies, oral administration of lazertinib to pregnant animals during the period of organogenesis resulted in reduced embryo-fetal survival and fetal body weight in rats and malformations in rabbits at exposures approximately 4 and 0.5 times, respectively, the human exposure at the recommended dose of 240 mg/day based on AUC.

Advise pregnant women and females of reproductive potential of the potential risk to a fetus. Advise females of reproductive potential to use effective contraception during treatment with LAZCLUZE and for 3 weeks after the last dose. Advise male patients with female partners of reproductive potential to use effective contraception during treatment with LAZCLUZE and for 3 weeks after the last dose [see Use in Specific Populations (8.1, 8.3)].

6 ADVERSE REACTIONS

The following adverse reactions are discussed elsewhere in the labeling:

- Venous Thromboembolic Events [see Warnings and Precautions (5.1)]
- Interstitial Lung Disease/Pneumonitis [see Warnings and Precautions (5.2)]
- Dermatologic Adverse Reactions [see Warnings and Precautions (5.3)]
- Ocular Toxicity [see Warnings and Precautions (5.4)]

6.1 Clinical Trials Experience

Because clinical trials are conducted under widely varying conditions, adverse reaction rates observed in the clinical trials of a drug cannot be directly compared to rates in the clinical trials of another drug and may not reflect the rates observed in practice.

The data described in WARNINGS AND PRECAUTIONS and below reflect exposure to LAZCLUZE in combination with amivantamab in 421 previously untreated patients with locally advanced or metastatic NSCLC whose tumors have EGFR exon 19 deletions or exon 21 L858R substitution mutations in MARIPOSA [see Clinical Studies (14)] . Patients received LAZCLUZE 240 mg orally once daily in combination with amivantamab intravenously at 1,050 mg (for patients < 80 kg) or 1,400 mg (for patients ≥ 80 kg) once weekly for 4 weeks, then every 2 weeks thereafter starting at week 5. Among the 421 patients who received LAZCLUZE in combination with amivantamab, 84% were exposed to LAZCLUZE for ≥ 6 months and 73% were exposed to LAZCLUZE for > 1 year.

The median age of patients who received LAZCLUZE in combination with amivantamab was 64 years (25 to 88); 64% were female; 59% were Asian, 38% were White, 1.7% were American Indian or Alaska Native, 0.7% were Black or African American, 1% were of unknown or other races; 13% were Hispanic or Latino; 67% had Eastern Cooperative Oncology Group (ECOG) performance status (PS) of 1, 33% had ECOG PS of 0; 60% had EGFR exon 19 deletions, and 40% had EGFR exon 21 L858R substitution mutations.

Serious adverse reactions occurred in 49% of patients who received LAZCLUZE in combination with amivantamab. Serious adverse reactions occurring in ≥ 2% of patients included VTE (11%), pneumonia (4%), rash and ILD/pneumonitis (2.9% each), COVID-19 (2.4%), and pleural effusion and infusion-related reaction (amivantamab) (2.1% each). Fatal adverse reactions occurred in 7% of patients who received LAZCLUZE in combination with amivantamab due to death not otherwise specified (1.2%); sepsis and respiratory failure (1% each); pneumonia, myocardial infarction, and sudden death (0.7% each); cerebral infarction, pulmonary embolism (PE), and COVID-19 infection (0.5% each); and ILD/pneumonitis, acute respiratory distress syndrome (ARDS), and cardiopulmonary arrest (0.2% each).

Permanent discontinuation of LAZCLUZE due to an adverse reaction occurred in 21% of patients. Adverse reactions which resulted in permanent discontinuation of LAZCLUZE in ≥ 1% of patients included ILD/pneumonitis, pneumonia, VTE, rash, respiratory failure, and sudden death.

Dosage interruption of LAZCLUZE due to an adverse reaction occurred in 72% of patients. Adverse reactions which required dosage interruption in ≥ 5% of patients were rash, nail toxicity, COVID-19, VTE, increased ALT, and increased AST.

Dose reductions of LAZCLUZE due to an adverse reaction occurred in 42% of patients. Adverse reactions requiring LAZCLUZE dose reductions in ≥ 5% of patients were rash and nail toxicity.

The most common adverse reactions (≥ 20%) were rash, nail toxicity, infusion-related reaction (amivantamab), musculoskeletal pain, edema, stomatitis, VTE, paresthesia, fatigue, diarrhea, constipation, COVID-19, hemorrhage, dry skin, decreased appetite, pruritus, and nausea. The most common Grade 3 or 4 laboratory abnormalities (≥ 2%) were decreased albumin, decreased sodium, increased ALT, decreased potassium, decreased hemoglobin, increased AST, increased GGT, and increased magnesium.

Table 3 summarizes the adverse reactions (≥ 10%) in MARIPOSA.

Table 3: Adverse Reactions (≥ 10%) in Patients with NSCLC with Exon 19 Deletion or Exon 21 L858R Substitution Mutations in MARIPOSA
Adverse Reaction | LAZCLUZE in combination with amivantamab (N=421) |  | Osimertinib (N=428)
 | All Grades (%) | Grade 3 or 4 (%) | All Grades (%) | Grade 3 or 4 (%)
Skin and subcutaneous tissue disorders
Rash [Grouped terms] | 86 | 26 | 48 | 1.2
Nail toxicity | 71 | 11 | 34 | 0.7
Dry skin | 25 | 1 | 18 | 0.2
Pruritus | 24 | 0.5 | 17 | 0.2
Injury, poisoning and procedural complications
Infusion-related reaction [Applicable only to amivantamab] | 63 | 6 | 0 | 0
Musculoskeletal and connective tissue disorders
Musculoskeletal pain | 47 | 2.1 | 39 | 1.9
Gastrointestinal disorders
Stomatitis | 43 | 2.4 | 27 | 0.5
Diarrhea | 31 | 2.6 | 45 | 0.9
Constipation | 29 | 0 | 13 | 0
Nausea | 21 | 1.2 | 14 | 0.2
Vomiting | 12 | 0.5 | 5 | 0
Abdominal pain | 11 | 0 | 10 | 0
Hemorrhoids | 10 | 0.2 | 2.1 | 0.2
General disorders and administration site conditions
Edema | 43 | 2.6 | 8 | 0
Fatigue | 32 | 3.8 | 20 | 1.9
Pyrexia | 12 | 0 | 9 | 0
Vascular disorders
Venous thromboembolism | 36 | 11 | 8 | 2.8
Hemorrhage | 25 | 1 | 13 | 1.2
Nervous system disorders
Paresthesia | 35 | 1.7 | 10 | 0.2
Dizziness | 14 | 0 | 10 | 0
Headache | 13 | 0.2 | 13 | 0
Infections and infestations
COVID-19 | 26 | 1.7 | 24 | 1.4
Conjunctivitis | 11 | 0.2 | 1.6 | 0
Metabolism and nutrition disorders
Decreased appetite | 24 | 1 | 18 | 1.4
Respiratory, thoracic and mediastinal disorders
Cough | 19 | 0 | 23 | 0
Dyspnea | 14 | 1.7 | 17 | 3.5
Eye disorders
Ocular toxicity | 16 | 0.7 | 7 | 0
Psychiatric disorders
Insomnia | 10 | 0 | 11 | 0

Clinically relevant adverse reactions occurring in < 10% of patients who received LAZCLUZE in combination with amivantamab included skin ulcer (applicable to amivantamab) and ILD/pneumonitis.

Table 4 summarizes the laboratory abnormalities in MARIPOSA.

Table 4: Select Laboratory Abnormalities (≥ 20%) That Worsened from Baseline in Patients with NSCLC with EGFR Exon 19 Deletion or Exon 21 L858R Substitution Mutations in MARIPOSA [The denominator used to calculate the rate is the number of patients with a baseline value and at least one post-treatment value for the specific lab test.]
Laboratory Abnormality | LAZCLUZE in combination with amivantamab (N=421) |  | Osimertinib (N=428)
 | All Grades (%) | Grade 3 or 4 (%) | All Grades (%) | Grade 3 or 4 (%)
Chemistry
Decreased albumin | 89 | 8 | 22 | 0.2
Increased ALT | 65 | 7 | 29 | 2.6
Increased AST | 52 | 3.8 | 36 | 1.9
Increased alkaline phosphatase | 45 | 0.5 | 15 | 0.5
Decreased calcium (corrected) | 41 | 1.4 | 27 | 0.7
Increased GGT | 39 | 2.6 | 24 | 1.9
Decreased sodium | 38 | 7 | 35 | 5
Decreased potassium | 30 | 5 | 15 | 1.2
Increased creatinine | 26 | 0.7 | 35 | 0.7
Decreased magnesium | 25 | 0.7 | 10 | 0.2
Increased magnesium | 12 | 2.6 | 20 | 4.8
Hematology
Decreased platelet count | 52 | 0.7 | 57 | 1.4
Decreased hemoglobin | 47 | 3.8 | 56 | 1.9
Decreased white blood cell | 38 | 1.0 | 66 | 0.7
Decreased neutrophils | 15 | 1.4 | 33 | 1.4

7 DRUG INTERACTIONS

7.1 Effect of Other Drugs on LAZCLUZE

CYP3A4 Inducers

Avoid concomitant use of LAZCLUZE with strong and moderate CYP3A4 inducers. Consider an alternate concomitant medication with no potential to induce CYP3A4.

Lazertinib is a CYP3A4 substrate. Concomitant use with a strong or moderate CYP3A4 inducer decreased lazertinib concentrations [see Clinical Pharmacology (12.3)] , which may reduce the efficacy of lazertinib.

7.2 Effect of LAZCLUZE on Other Drugs

Certain CYP3A4 Substrates

Monitor for adverse reactions associated with a CYP3A4 substrate where minimal concentration changes may lead to serious adverse reactions, as recommended in the approved product labeling for the CYP3A4 substrate.

Lazertinib is a weak CYP3A4 inhibitor. Concomitant use of LAZCLUZE increased concentrations of CYP3A4 substrates [see Clinical Pharmacology (12.3)] , which may increase the risk of adverse reactions related to these substrates.

Certain BCRP Substrates

Monitor for adverse reactions associated with a BCRP substrate where minimal concentration changes may lead to serious adverse reactions, as recommended in the approved product labeling for the BCRP substrate.

Lazertinib is a BCRP inhibitor. Concomitant use of LAZCLUZE increased concentrations of BCRP substrates [see Clinical Pharmacology (12.3)], which may increase the risk of adverse reactions related to these substrates.

8 USE IN SPECIFIC POPULATIONS

8.1 Pregnancy

Risk Summary

Based on findings from animal studies and its mechanism of action [see Clinical Pharmacology (12.1)] , LAZCLUZE can cause fetal harm when administered to a pregnant woman. There are no available data on the use of LAZCLUZE in pregnant women to inform a drug-associated risk. Oral administration of lazertinib to pregnant animals during the period of organogenesis resulted in reduced embryo-fetal survival and fetal body weight in rats and malformations in rabbits at exposures approximately 4 and 0.5 times, respectively, the human exposure at the recommended dose of 240 mg/day based on AUC (see Data) . Advise pregnant women of the potential risk to a fetus.

In the U.S. general population, the estimated background risk of major birth defects and miscarriage in clinically recognized pregnancies is 2% to 4% and 15% to 20%, respectively.

Data

Animal Data

In an embryo-fetal development study, pregnant rats received oral doses of 7.5, 30, or 60 mg/kg/day of lazertinib during the period of organogenesis (gestation day 6 to 17). Lazertinib decreased fetal body weights in association with maternal toxicity at 60 mg/kg/day (approximately 4 times the human exposure at the recommended dose of 240 mg/day based on AUC). In a dose range-finding embryo-fetal development study, oral administration of a higher dose of lazertinib (75 mg/kg/day) to pregnant rats during the period of organogenesis resulted in increased post-implantation loss. In an embryo-fetal development study in rabbits, pregnant animals received oral doses of 5, 25, or 45 mg/kg/day of lazertinib during the period of organogenesis (gestation day 7 to 19). Lazertinib caused maternal toxicity (reduced body weight and food consumption leading to moribund condition and early termination) and an increase in the incidence of skeletal malformations in the vertebra and skull (fused maxillary process/zygomatic arch) at 45 mg/kg/day (approximately 0.5 times the human exposure at the recommended dose of 240 mg/day based on AUC).

8.2 Lactation

Risk Summary

There are no data on the presence of lazertinib or its metabolites in human milk or their effects on the breastfed child or on milk production. Because of the potential for serious adverse reactions in breastfed children, advise women not to breastfeed during treatment with LAZCLUZE and for 3 weeks after the last dose. Refer to the amivantamab prescribing information for lactation information during treatment with amivantamab.

8.3 Females and Males of Reproductive Potential

Based on animal data and its mechanism of action, LAZCLUZE can cause fetal harm when administered to a pregnant woman [see Use in Specific Populations (8.1)] .

Pregnancy Testing

Verify the pregnancy status of females of reproductive potential prior to initiating LAZCLUZE.

Contraception

Females

Advise females of reproductive potential to use effective contraception during treatment with LAZCLUZE and for 3 weeks after the last dose. Refer to the amivantamab prescribing information for recommended duration of contraception during treatment with amivantamab.

Males

Advise male patients with female partners of reproductive potential to use effective contraception during treatment with LAZCLUZE and for 3 weeks after the last dose.

Infertility

Based on findings in animals, LAZCLUZE may impair fertility in females and males of reproductive potential. The effects on female fertility were reversible. The effects on male testes in animal studies were not reversible within a 2-week recovery period [see Nonclinical Toxicology (13.1)].

8.4 Pediatric Use

The safety and effectiveness of LAZCLUZE in pediatric patients have not been established.

8.5 Geriatric Use

Of the 421 patients with locally advanced or metastatic NSCLC treated with LAZCLUZE in combination with amivantamab in MARIPOSA, 45% were 65 years and older and 12% were 75 years and older. No overall differences in safety or effectiveness were observed between patients aged 65 and older and younger patients.

8.6 Renal Impairment

No dose adjustment is recommended in patients with mild or moderate renal impairment (eGFR 30 – 89 mL/min) [see Clinical Pharmacology (12.3)] .

LAZCLUZE has not been studied in patients with severe renal impairment or end-stage renal disease (eGFR < 30 mL/min).

8.7 Hepatic Impairment

No dose adjustment is recommended in patients with mild (total bilirubin ≤ ULN and AST > ULN or total bilirubin ≤ 1.5×ULN and any AST) or moderate (total bilirubin ≤ 1.5 to 3×ULN and any AST) hepatic impairment [see Clinical Pharmacology (12.3)] .

LAZCLUZE has not been studied in patients with severe hepatic impairment (total bilirubin > 3×ULN and any AST).

11 DESCRIPTION

LAZCLUZE®tablets contain lazertinib, a kinase inhibitor for oral use. Lazertinib is present as lazertinib mesylate hydrate with a molecular weight of 668.77 and molecular formula of C30H34N8O3∙CH4O3S∙H2O. The chemical name is N-[5-[[4-[4-[(Dimethylamino)methyl]-3-phenyl-1 H-pyrazol-1-yl]pyrimidin-2-yl]amino]-4-methoxy-2-(morpholin-4-yl)phenyl]acrylamide methanesulfonate hydrate (1:1:1). Lazertinib mesylate hydrate is soluble or practically insoluble in aqueous media, and slightly soluble to freely soluble in organic solvents over a wide range of pH values. The structural formula is:

LAZCLUZE (lazertinib) film-coated tablets contain 80 mg or 240 mg of lazertinib, equivalent to 93.86 and 281.58 mg lazertinib mesylate (calculated on anhydrous basis), respectively. The inactive ingredients are croscarmellose sodium, magnesium stearate, mannitol, microcrystalline cellulose, and silica hydrophobic colloidal. The tablet coating consists of glycerol monocaprylocaprate type I, iron oxide black (in 240 mg strength tablets), iron oxide red (in 240 mg strength tablets), iron oxide yellow (in 80 mg strength tablets), macrogol (PEG) polyvinyl alcohol graft copolymer, polyvinyl alcohol-partially hydrolyzed, talc, and titanium dioxide.

12 CLINICAL PHARMACOLOGY

12.1 Mechanism of Action

Lazertinib is a kinase inhibitor of epidermal growth factor receptor (EGFR) that inhibits EGFR exon 19 deletions and exon 21 L858R substitution mutations at lower concentrations than wild-type EGFR. In human NSCLC cells and mouse xenograft models of EGFR exon 19 deletions or EGFR L858R substitution mutations, lazertinib demonstrated anti-tumor activity. Treatment with lazertinib in combination with amivantamab increased in vivo anti-tumor activity compared to either agent alone in a mouse xenograft model of human NSCLC with an EGFR L858R mutation.

12.2 Pharmacodynamics

The exposure-response relationship and time-course of pharmacodynamic response of lazertinib have not been fully characterized.

Cardiac Electrophysiology

At a dose of 320 mg (1.3 times the approved recommended dosage) once daily, a mean increase in the QTc interval > 20 ms is unlikely.

12.3 Pharmacokinetics

Lazertinib pharmacokinetics are presented as mean (CV%) for descriptive parameters unless otherwise specified.

Lazertinib maximum plasma concentration (Cmax) and area under plasma concentration time curve (AUC) increased dose proportionally from 20 mg to 320 mg (0.08 to 1.3 times the approved recommended dosage) following a single administration and once daily administration. Lazertinib steady state plasma exposure was achieved by day 15 with approximately 2-fold accumulation for AUC.

Absorption

The median time to reach Cmaxis from 2 to 4 hours.

Effect of Food

A high-fat meal (800 to 1000 kcal, approximately 50% fat) did not have a clinically significant effect on lazertinib pharmacokinetics compared to that under fasted conditions.

Distribution

The mean apparent volume of distribution is 2680 L (51%).

Lazertinib is approximately 99.2% bound to human plasma proteins.

Elimination

The mean terminal half-life is 3.7 days (56%).

The mean apparent clearance is 36.4 L/h (47%).

Metabolism

Lazertinib is primarily metabolized by glutathione conjugation, either enzymatic via glutathione-S-transferase (GST) or non-enzymatic, as well as by CYP3A4.

Excretion

Following a single oral dose of radiolabeled lazertinib, approximately 86% of the dose was recovered in feces (< 5% as unchanged) and 4% in urine (< 0.2% as unchanged).

Specific Populations

No clinically significant differences in pharmacokinetics of lazertinib were observed based on age (21 to 88 years), sex, body weight (28 to 122 kg), race (White, Asian, Black or African American), ethnicity (Hispanic/Latino or not Hispanic/Latino), baseline laboratory assessments (creatinine clearance, albumin, alanine aminotransferase, alkaline phosphatase, aspartate aminotransferase), mild or moderate renal impairment (eGFR 30 to 89 mL/min, estimated by CKD-EPI equation), mild [total bilirubin ≤ ULN and AST > ULN or total bilirubin ≤ 1.5 times ULN and any AST] or moderate [total bilirubin ≤ 1.5 to 3×ULN and any AST] hepatic impairment, ECOG performance status, EGFR mutation type, initial diagnosis cancer stage, prior therapies, brain metastasis, and history of smoking.

The effect of severe renal impairment (eGFR 15 to 29 mL/min), end-stage renal disease (eGFR < 15 mL/min) or severe hepatic impairment (total bilirubin > 3 times ULN with any AST) on the pharmacokinetics of lazertinib has not been studied.

GSTM1 Genotype

Patients with at least one GSTM1 normal function allele have 44% lower systemic levels of lazertinib compared with those with the two GSTM1 no-function alleles (i.e., no enzyme activity). No clinically significant differences in safety or efficacy were observed as a function of GSTM1 genotype in patients receiving LAZCLUZE in combination with amivantamab.

Drug Interactions

Clinical Studies and Model-Informed Approaches

Effect of CYP3A4 inducers on lazertinib:

Concomitant use of rifampin (strong CYP3A4 inducer) with LAZCLUZE decreased lazertinib Cmaxby 72% and AUC by 83%.

Concomitant use of efavirenz (moderate CYP3A4 inducer) with LAZCLUZE is predicted to decrease lazertinib steady state Cmaxby at least 32% and AUC by at least 44%.

The effect of concomitant use of weak CYP3A4 inducers on lazertinib Cmaxor AUC is unknown.

Effect of strong CYP3A4 inhibitors on lazertinib:

Concomitant use of itraconazole (strong CYP3A4 inhibitor) with LAZCLUZE increased lazertinib Cmaxby 1.2-fold and AUC by 1.5-fold.

Effect of gastric acid reducing agents on lazertinib:

No clinically significant differences in lazertinib Cmaxand AUC were observed when used concomitantly with gastric acid reducing agents.

Effect of lazertinib on certain CYP3A4 substrates:

Concomitant use of LAZCLUZE increased midazolam (CYP3A4 substrate) Cmaxby 1.4-fold and AUC by 1.5-fold.

Effect of lazertinib on BCRP substrates:

Concomitant use of LAZCLUZE increased rosuvastatin (BCRP substrate) Cmaxby 2.2-fold and AUC by 2-fold.

No clinically significant differences in the pharmacokinetics of the following were observed or predicted when used concomitantly with lazertinib: metformin (OCT1 substrate) or raltegravir (UGT1A1 substrate).

In Vitro Studies

Lazertinib inhibits CYP3A4, UGT1A1, BCRP and OCT1. Lazertinib does not induce CYP1A2, CYP2B6 and CYP3A4.

13 NONCLINICAL TOXICOLOGY

13.1 Carcinogenesis, Mutagenesis, Impairment of Fertility

Carcinogenicity studies have not been conducted with lazertinib.

Lazertinib was not genotoxic in an in vitro bacterial reverse mutation (Ames) assay, an in vitro chromosomal aberration assay, or an in vivo micronucleus assay in rats.

In a dedicated fertility and early embryonic development study, male and female rats received oral doses of 7.5, 15, or 30 mg/kg/day of lazertinib. Males were dosed for 10 weeks (29 days prior to pairing, during mating period and continuing post-pairing). Females were dosed for 15 days prior to pairing, during mating period and up to Gestation Day 7. Lazertinib did not have clear effects on estrous cyclicity, mating, fertility, or sperm parameters, but induced an increase in post-implantation loss and decreased number of live fetuses at 30 mg/kg/day (approximately 1.2 times the recommended human dose of 240 mg based on body surface area). In repeat-dose oral general toxicology studies up to 13-weeks duration, lazertinib induced histologic tubular degeneration in the testis; cellular lumen debris, degeneration/necrosis, and reduced sperm in the epididymis; decreased corpora lutea in the ovary; and atrophy in the uterus and vagina. These effects were observed at exposures approximately equivalent to the human exposure at the recommended dose of 240 mg in males, and at exposures approximately 2 times the human exposure at the recommended dose of 240 mg dose in females. Findings in female reproductive organs were reversible. The tubular degeneration in the testis observed in rats at exposures approximately 4 times the human exposure at the recommended dose was not reversible within a 2-week recovery period.

13.2 Animal Toxicology and/or Pharmacology

In repeat-dose oral general toxicology studies up to 13-weeks duration in rats and dogs, lazertinib induced multi-organ histologic hyperplasia at exposures approximately equivalent or greater to the human exposure at the recommended dose of 240 mg. Hyperplasia was not reversible in the mandibular lymph node in the 4-week rat study. In rats, lazertinib induced renal toxicity characterized by histologic hyperplasia and inflammation in the kidney at doses ≥ 25 mg/kg (approximately 0.9 times the human exposure at the recommended dose of 240 mg/day based on AUC), along with increased urea nitrogen and histologic papillary necrosis, tubule degeneration/regeneration, and tubule dilatation at exposures approximately 4.4 times the human exposure at the recommended dose of 240 mg/day based on AUC. Increased urea nitrogen, papillary necrosis, and tubule dilatation showed evidence of recovery. In the 13-week toxicology study in dogs, one high dose animal exhibited unilateral tubule cell renal carcinoma at 8 mg/kg/day (approximately 2 times the human exposure at the recommended dose of 240 mg/day based on AUC). Other renal findings in high dose dogs included tubule degeneration/regeneration and infarct, which showed evidence of recovery. In the 4-week toxicology study, lazertinib induced cardiac toxicity in two dogs characterized by histologic findings in the heart (degeneration/necrosis of the myocardium and vessels, fibrosis, hemorrhage, thrombus, mixed cell/vessel inflammation) at 20 mg/kg (approximately 4.8 times the clinical AUC at the 240 mg human dose). One of these dogs also exhibited increased cardiac troponin I and premature ventricular complexes. These cardiac findings were not seen after a 2-week recovery period.

14 CLINICAL STUDIES

The efficacy of LAZCLUZE, in combination with amivantamab, was evaluated in MARIPOSA [NCT04487080], a randomized, active-controlled, multicenter trial. Eligible patients were required to have untreated locally advanced or metastatic NSCLC with either exon 19 deletions or exon 21 L858R substitution EGFR mutations identified by local testing, not amenable to curative therapy. Patients with asymptomatic or previously treated and stable intracranial metastases were eligible to enroll.

Patients were randomized (2:2:1) to receive LAZCLUZE in combination with amivantamab (N=429), osimertinib monotherapy (N=429), or LAZCLUZE monotherapy (an unapproved regimen for NSCLC) until disease progression or unacceptable toxicity. The evaluation of efficacy for the treatment of untreated metastatic NSCLC relied upon comparison between:

- LAZCLUZE administered at 240 mg orally once daily in combination with amivantamab administered intravenously at 1050 mg (for patients < 80 kg) or 1400 mg (for patients ≥ 80 kg) once weekly for 4 weeks, then every 2 weeks thereafter starting at week 5.
- Osimertinib administered at a dose of 80 mg orally once daily.

Randomization was stratified by EGFR mutation type (exon 19 deletion or exon 21 L858R substitution mutation), Asian race (yes or no), and history of brain metastasis (yes or no). Tumor assessments were performed every 8 weeks for 30 months, and then every 12 weeks until disease progression.

The major efficacy outcome measure was progression-free survival (PFS) as assessed by blinded independent central review (BICR). Additional efficacy outcome measures included overall survival (OS), overall response rate (ORR) and duration of response (DOR).

A total of 858 patients were randomized between the two study arms, 429 to the LAZCLUZE in combination with amivantamab arm and 429 to the osimertinib arm. The median age was 63 (range: 25–88) years; 61% were female; 58% were Asian, and 38% were White, 1.6% were American Indian or Alaska Native, 0.8% were Black or African American, 0.2% were Native Hawaiian or other Pacific Islander, 0.6% were unknown race or multiple races; and 12% were Hispanic or Latino. Eastern Cooperative Oncology Group (ECOG) performance status was 0 (34%) or 1 (66%); 69% never smoked; 41% had prior brain metastases; and 89% had Stage IV cancer at initial diagnosis. Sixty percent of patients had tumors harboring exon 19 deletions and the remaining 40% had exon 21 L858R substitution mutations.

Among the 858 patients with EGFR exon 19 deletion or L858R substitution mutations that were randomized between the amivantamab plus LAZCLUZE arm versus the osimertinib arm, available tissue samples from 544 (63%) patients had evaluable results when tested retrospectively using the cobas EGFR Mutation Test v2. Of the 544 patients with evaluable results, 527 (97%) patients were positive for EGFR exon 19 deletion or L858R substitution mutations, while 17 (3%) patients were negative. Available plasma samples from patients were retrospectively tested using an FDA-approved test to confirm the biomarker status.

The trial demonstrated a statistically significant improvement in PFS by BICR assessment and OS for LAZCLUZE in combination with amivantamab compared to osimertinib (see Table 5and Figures 1and 2).

Efficacy results are provided in Table 5.

Table 5: Efficacy Results in MARIPOSA by BICR Assessment
 | LAZCLUZE in combination with amivantamab (N=429) | Osimertinib (N=429)
Progression-free survival (PFS)
Number of events (%) | 192 (45) | 252 (59)
Median, months (95% CI) | 23.7 (19.1, 27.7) | 16.6 (14.8, 18.5)
HR [Stratified by mutation type (Exon 19del or Exon 21 L858R), prior brain metastases (yes or no), and Asian race (yes or no).] , [Stratified Cox proportional hazards regression.] (95% CI); p-value , [Stratified log-rank test.] | 0.70 (0.58, 0.85); p=0.0002
Overall survival (OS)
Number of events (%) | 173 (40) | 217 (51)
Median, months (95% CI) | NR (42.9, NE) | 36.7 (33.4, 41.0)
HR ,(95% CI); p-value , | 0.75 (0.61, 0.92); p=0.0048
Overall response rate (ORR) [Confirmed responses based on the ITT population.]
ORR, % (95% CI) | 78 (74, 82) | 73 (69, 78)
Complete response, % | 5 | 3.5
Partial response, % | 73 | 70
Duration of response (DOR) [In confirmed responders.]
Median (95% CI), months | 25.8 (20.1, NE) | 16.7 (14.8, 18.5)
Patients with DOR ≥ 6 months [Based on observed rates.] , % | 86 | 85
Patients with DOR ≥ 12 months , % | 68 | 57
CI = confidence interval; NR = not reached; NE = not estimable

Figure 1: Kaplan-Meier Curves of PFS by BICR Assessment in Patients with Previously Untreated NSCLC

Figure 2: Kaplan-Meier Curves of OS in Patients with Previously Untreated NSCLC

Out of all randomized patients (n=858), 367 (43%) had baseline intracranial lesions assessed by BICR using modified RECIST. Results of pre-specified analyses of intracranial ORR and DOR by BICR in the subset of patients with intracranial lesions at baseline for the LAZCLUZE in combination with amivantamab arm and the osimertinib arm are summarized in Table 6.

Table 6: Exploratory Analysis of Intracranial ORR and DOR by BICR Assessment in Subjects with Intracranial Lesions at Baseline
 | LAZCLUZE in combination with amivantamab (N=180) | Osimertinib (N=187)
Intracranial Tumor Response Assessment
Intracranial ORR [Confirmed responses] , % (95% CI) | 68 (60, 75) | 69 (62, 76)
Complete response, % | 55 | 52
Intracranial DOR [In confirmed responders]
Number of responders | 122 | 129
Patients with DOR ≥ 12 months [Based on observed rates] , % | 66 | 59
Patients with DOR ≥ 18 months , % | 35 | 23
CI = confidence interval

16 HOW SUPPLIED/STORAGE AND HANDLING

LAZCLUZE®(lazertinib) tablets are available in the strengths and packages listed below:

Tablet Strength | Description | Package Configuration | NDC Number
80 mg | Yellow, oval, film-coated, debossed with "LZ" on one side and "80" on the other side | 60-count bottle | NDC 57894-080-60
240 mg | Reddish purple, oval, film-coated, debossed with "LZ" on one side and "240" on the other side | 30-count bottle | NDC 57894-240-30

STORAGE AND HANDLING

Store at 20°C to 25°C (68°F to 77°F); excursions permitted between 15°C to 30°C (59°F to 86°F) [see USP Controlled Room Temperature].

17 PATIENT COUNSELING INFORMATION

Advise the patient to read the FDA-approved patient labeling (Patient Information).

Venous Thromboembolic Events

Advise patients of the risks of serious and life threatening venous thromboembolic events (VTE), including deep venous thrombosis and pulmonary embolism. Advise patients that prophylactic anticoagulants are recommended to be used for the first four months of treatment. Advise patients to immediately contact their healthcare provider for signs and symptoms of venous thromboembolism [see Warnings and Precautions (5.1)] .

Interstitial Lung Disease/Pneumonitis

Advise patients of the risks of interstitial lung disease (ILD)/pneumonitis. Advise patients to immediately contact their healthcare provider for new or worsening respiratory symptoms [see Warnings and Precautions (5.2)] .

Dermatologic Adverse Reactions

Advise patients of the risk of dermatologic adverse reactions. Advise patients that prophylactic oral antibiotics are recommended starting on Day 1 for the first 12 weeks of treatment and, after completion of oral antibiotic treatment, topical antibiotic lotion to the scalp for the next 9 months of treatment. Advise patients to use non-comedogenic skin moisturizer (ceramide-based or other formulations that provide long-lasting skin hydration and exclude drying components) on the face and whole body (except scalp) and 4% chlorhexidine solution to wash hands and feet, while on treatment. Advise patients to limit direct sun exposure during and for 2 months after treatment, to wear protective clothing, and to use broad-spectrum UVA/UVB sunscreen to reduce the risk and severity of dermatologic adverse reactions [see Warnings and Precautions (5.3)].

Ocular Toxicity

Advise patients of the risk of ocular adverse reactions. Advise patients to contact their ophthalmologist if they develop eye symptoms. Advise discontinuation of contact lenses until symptoms are evaluated [see Warnings and Precautions (5.4)] .

Embryo-Fetal Toxicity

Advise females of reproductive potential of the potential risk to a fetus, to use effective contraception during treatment with LAZCLUZE and for 3 weeks after the last dose, and to inform their healthcare provider of a known or suspected pregnancy [see Warnings and Precautions (5.5), Use in Specific Populations (8.1, 8.3)]. Refer to the amivantamab prescribing information for recommended duration of contraception during treatment with amivantamab.

Advise male patients with female partners of reproductive potential to use effective contraception during treatment with LAZCLUZE and for 3 weeks after the last dose [see Use in Specific Populations (8.3)].

Lactation

Advise women not to breastfeed during treatment with LAZCLUZE and for 3 weeks after the last dose [see Use in Specific Populations (8.2)] . Refer to the amivantamab prescribing information for lactation information during treatment with amivantamab.

Infertility

Advise males and females of reproductive potential of the potential risk for impaired fertility with LAZCLUZE [see Nonclinical Toxicology (13.1)] .

Product of Belgium

Manufactured for:
Janssen Biotech, Inc.
Horsham, PA 19044, USA

For patent information: www.janssenpatents.com

© Johnson & Johnson and its affiliates 2024–2025

PATIENT INFORMATION
LAZCLUZE ® (laz-kluez)
(lazertinib)
tablets, for oral use

What is LAZCLUZE?
LAZCLUZE in combination with amivantamab is a prescription medicine for the first-line treatment of adults with non-small cell lung cancer (NSCLC) that:

- has spread to other parts of the body (metastatic) or cannot be removed by surgery, and
- has a certain abnormal epidermal growth factor receptor "EGFR" gene(s).

Your healthcare provider will perform a test to make sure that LAZCLUZE is right for you.
It is not known if LAZCLUZE is safe and effective in children.

Before taking LAZCLUZE, tell your healthcare provider about all of your medical conditions, including if you:

- have a history of lung or breathing problems
- are pregnant or plan to become pregnant. LAZCLUZE can harm your unborn baby.
  Females who are able to become pregnant:
  - Your healthcare provider should do a pregnancy test before you start treatment with LAZCLUZE.
  - You should use effective birth control (contraception) during treatment and for 3 weeks after your last dose of LAZCLUZE.
  - Tell your healthcare provider right away if you become pregnant or think you might be pregnant during treatment with LAZCLUZE.
  Males who have female partners who are able to become pregnant:
  - You should use effective birth control during treatment and for 3 weeks after your last dose of LAZCLUZE.
- are breastfeeding or plan to breastfeed. It is not known if LAZCLUZE passes into your breast milk. Do not breastfeed during treatment and for 3 weeks after your last dose of LAZCLUZE.

Tell your healthcare provider about all the medicines you take, including prescription and over-the-counter medicines, vitamins, and herbal supplements.
LAZCLUZE may affect the way other medicines work, and other medicines may affect how LAZCLUZE works.
You should not start or stop any medicine before you talk with your healthcare provider that prescribed LAZCLUZE.

How should I take LAZCLUZE?

- Take LAZCLUZE exactly as your healthcare provider tells you to take it.
- Take LAZCLUZE 1-time each day. On the day amivantamab is also given, take LAZCLUZE any time before receiving the amivantamab infusion.
- You can take LAZCLUZE with or without food.
- Swallow LAZCLUZE tablets whole. Do not crush, cut, or chew the tablets.
- If you miss a dose of LAZCLUZE and:
  - it has been less than 12 hours, take the missed dose.
  - it has been more than 12 hours, skip the dose and take your next dose at your regularly scheduled time.
- If you vomit a dose of LAZCLUZE, do not take an extra dose. Take your next dose at your regularly scheduled time.
- Your healthcare provider may give you medicines in addition to LAZCLUZE to reduce the risk and severity of skin and nail reactions.
- LAZCLUZE may be given in combination with other anti-cancer medicines. If you have any questions about these medicines, ask your healthcare provider.

What should I avoid while taking LAZCLUZE?
LAZCLUZE can cause skin reactions. You should limit your time in the sun during and for 2 months after your treatment with LAZCLUZE. Wear protective clothing and use broad-spectrum UVA/UVB sunscreen during treatment with LAZCLUZE.

What are the possible side effects of LAZCLUZE?
LAZCLUZE may cause serious side effects, including:

- blood clot problems. Blood clots in the veins of your legs (deep vein thrombosis) or lungs (pulmonary embolism) are serious, but common, and may lead to death. Your healthcare provider will start you on medicine to reduce the risk of blood clots for the first four months of treatment. Tell your healthcare provider right away if you have any signs and symptoms of blood clots, including swelling, pain or tenderness in the leg, sudden unexplained chest pain, or shortness of breath.
- lung problems. LAZCLUZE may cause lung problems that may lead to death. Symptoms may be similar to those symptoms from lung cancer. Tell your healthcare provider right away if you get any new or worsening lung symptoms, including shortness of breath, cough, or fever.
- skin problems. LAZCLUZE may cause severe rash including redness, raised acne-like bumps, itching, and dry skin. Tell your healthcare provider right away if you get any skin reactions. Your healthcare provider may start you on an antibiotic for the first 3 months of treatment followed by an antibiotic lotion for your scalp for the next 9 months. During treatment with LAZCLUZE, you should apply a non-comedogenic (does not clog pores) skin moisturizer (ceramide-based or other types of moisturizers that provide long-lasting skin hydration and does not include drying ingredients) on your face and whole body (except scalp) and wash your hands and feet every day with 4% chlorhexidine solution. Your healthcare provider may treat you with a medicine(s) or send you to see a skin specialist (dermatologist) if you get skin reactions during treatment with LAZCLUZE. See " What should I avoid while taking LAZCLUZE?"
- eye problems. LAZCLUZE may cause eye problems such as inflamed cornea (front part of your eye). Tell your healthcare provider right away if you get symptoms such as eye redness, eye pain, new or worsening problems with vision, and sensitivity to light.

Your healthcare provider may send you to see an eye specialist (ophthalmologist) if you get eye problems during treatment with LAZCLUZE. You should not use contact lenses until your eye symptoms are checked by a healthcare provider.
The most common side effects of LAZCLUZE in combination with amivantamab include:

- rash
- infected skin around the nail
- infusion-related reaction (amivantamab)
- muscle and joint pain
- sores in the mouth
- swelling of hands, ankles, feet, face, or all of your body
- unusual feeling in the skin (such as tingling or crawling)

- feeling very tired
- diarrhea
- constipation
- COVID-19
- bleeding
- decreased appetite
- itchy skin
- nausea
- changes in certain blood tests

LAZCLUZE may cause fertility problems in males and females, which may affect your ability to have children. Talk to your healthcare provider if this is a concern for you.
Your healthcare provider may temporarily stop, decrease your dose or completely stop your treatment with LAZCLUZE if you have serious side effects.
These are not all of the possible side effects of LAZCLUZE.
Call your doctor for medical advice about side effects. You may report side effects to FDA at 1-800-FDA-1088.

How should I store LAZCLUZE?

- Store LAZCLUZE at room temperature between 68° F to 77° F (20° C to 25° C).

Keep LAZCLUZE and all medicines out of the reach of children.

General information about the safe and effective use of LAZCLUZE.
Medicines are sometimes prescribed for purposes other than those listed in a Patient Information leaflet. Do not use LAZCLUZE for a condition for which it was not prescribed. Do not give LAZCLUZE to other people, even if they have the same symptoms that you have. It may harm them.
You can ask your pharmacist or healthcare provider for information about LAZCLUZE that is written for health professionals.

What are the ingredients in LAZCLUZE?
Active ingredient : lazertinib mesylate
Inactive ingredients: croscarmellose sodium, magnesium stearate, mannitol, microcrystalline cellulose, and silica hydrophobic colloidal. The tablet coating consists of glycerol monocaprylocaprate type I, iron oxide black (in 240 mg strength tablets), iron oxide red (in 240 mg strength tablets), iron oxide yellow (in 80 mg strength tablets), macrogol (PEG) polyvinyl alcohol graft copolymer, polyvinyl alcohol-partially hydrolyzed, talc, and titanium dioxide.
Product of Belgium
Manufactured for: Janssen Biotech, Inc., Horsham, PA 19044, USA
For patent information: www.janssenpatents.com
© Johnson & Johnson and its affiliates 2024–2025
For more information, call 1-800-526-7736 or go to www.lazcluze.com

This Patient Information has been approved by the U.S. Food and Drug Administration.

Revised: 11/2025

PRINCIPAL DISPLAY PANEL - 240 mg Tablet Bottle Carton

NDC 57894-240-30

Lazcluze™
(lazertinib)
tablets

240 mg

Each film-coated tablet contains
240 mg of lazertinib equivalent
to 281.58 mg lazertinib mesylate
(on anhydrous basis).

Rx only

30 film-coated tablets

janssen

PRINCIPAL DISPLAY PANEL - 80 mg Tablet Bottle Carton

NDC 57894-080-60

Lazcluze™
(lazertinib)
tablets

80 mg

Each film-coated tablet contains
80 mg of lazertinib equivalent to
93.86 mg lazertinib mesylate
(on anhydrous basis).

Rx only

60 film-coated tablets

janssen